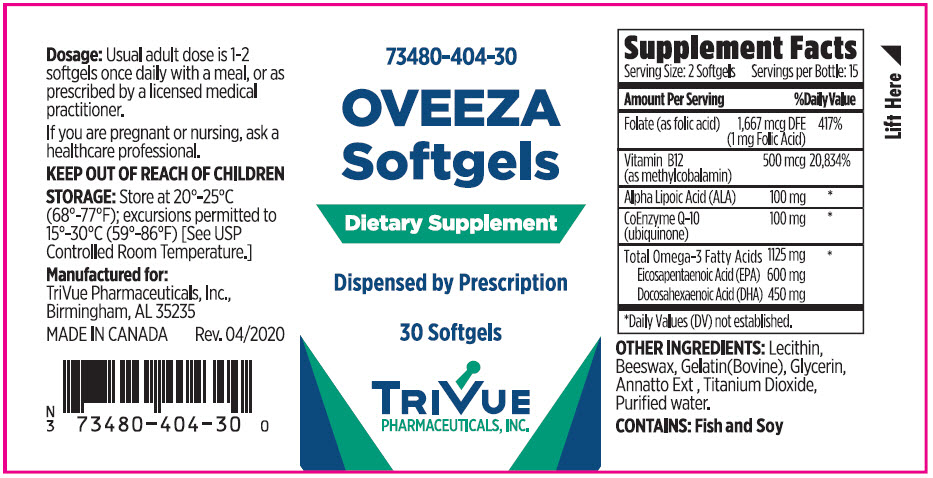 DRUG LABEL: Oveeza
NDC: 73480-404 | Form: CAPSULE, LIQUID FILLED
Manufacturer: TriVue Pharmaceuticals, Inc.
Category: other | Type: DIETARY SUPPLEMENT
Date: 20200506

ACTIVE INGREDIENTS: FOLIC ACID 0.5 mg/1 1; METHYLCOBALAMIN 250 ug/1 1; ALPHA LIPOIC ACID 50 mg/1 1; UBIDECARENONE 50 mg/1 1; OMEGA-3 FATTY ACIDS 563 mg/1 1; ICOSAPENT 300 mg/1 1; DOCONEXENT 225 mg/1 1
INACTIVE INGREDIENTS: HYDROGENATED SOYBEAN LECITHIN; Yellow Wax; GELATIN, UNSPECIFIED; GLYCERIN; ANNATTO; TITANIUM DIOXIDE; WATER

Oveeza

KEEP OUT OF REACH OF CHILDREN.

Manufactured for: TriVue Pharmaceuticals, Inc.Birmingham, AL 35235

This product is not an Orange Book product.
Dispensed by Prescription†
MADE IN CANADA
Rev. 04/2020*

STATEMENT OF IDENTITY

TriVue Pharmaceuticals does not represent these product codes to be National Drug Codes (NDC). Product codes are formatted according to standard industry practice, to meet the formatting requirement by pedigree reporting and supply-chain control including pharmacies.† This product is a prescription-folate with or without other dietary ingredients that – due to increased folate levels increased risk associated with masking of B12 deﬁciency (pernicious anemia) requires administration under the care of a licensed medical practitioner (61 FR 8760). 1-3 The most appropriate way to ensure pedigree reporting consistent with these regulatory guidelines and safety monitoring is to dispense this product only by prescription. This is not an Orange Book product. This product may be administered only under a physician's supervision and all prescriptions using this product shall be pursuant to state statutes as applicable. The ingredients, indication or claims of this product are not to be construed to be drug claims.1. Federal Register Notice of August 2, 1973 (38 FR 20750)2. Federal Register Notice of October 17, 1980 (45 FR 69043, 69044) 3. Federal Register Notice of March 5, 1996 (61 FR 8760)

Dosage

Usual adult dose is 1-2 softgels once daily with a meal, or as prescribed by a licensed medical practitioner.If you are pregnant or nursing, ask a healthcare professional.

KEEP OUT OF REACH OF CHILDREN

STORAGE

Store at 20°-25°C (68°-77°F); excursions permitted to 15°-30°C (59°-86°F) [See USP Controlled Room Temperature.]

HEALTH CLAIM

Manufactured for: TriVue Pharmaceuticals, Inc.,Birmingham, AL 35235

MADE IN CANADA Rev. 04/2020

DESCRIPTION

Oveeza Softgels is an orally administered prescription dietary supplement for the clinical dietary management of suboptimal nutritional status in patients where advanced folate, vitamin B, and Omega-3 supplementation, and maintenance of good health is needed.

CONTRAINDICATIONS

Oveeza Softgels are contraindicated in patients with a known hypersensitivity to any of the ingredients.

WARNINGS AND PRECAUTIONS

PRECAUTION

Use with caution in patients that may have a medical condition, planning surgery, have bleeding problems,are pregnant, lactating, trying to conceive, under the age of 18, or taking other medications. Folic acid alone is improper therapy in the treatment of pernicious anemia and other megaloblastic anemias where vitamin B12 is deﬁcient. Folic acid in doses above 0.1 mg daily may obscure pernicious anemia in that hematologic remission can occur while neurological manifestations progress. Oveeza Softgels should only be used under the direction and supervision of a licensed medical practitioner. Ingestion of more than 3 grams of omega-3 fatty acids (such as DHA and EPA) per day has been shown to have potential antithrombotic effects, including an increased bleeding time and International Normalized Ratio (INR). Administration of omega-3 fatty acids should be avoided in patients taking anticoagulants and in those known to have an inherited or acquired predisposition to bleeding.

Potential for Allergic Reactions in Patients with Fish Allergy: It is not known whether patients with allergies to ﬁsh and/or shellﬁsh are at increased risk of an allergic reaction to products containing omega-3 fatty acid ethyl esters, eicosapentaenoic acid (EPA) and docosahexaenoic acid (DHA), derived from ﬁsh oil. Inform patients with known hypersensitivity to ﬁsh and/or shellﬁsh about the potential for allergic reactions to Oveeza and advise them to discontinue and seek medical attention if any reactions occur.

ADVERSE REACTIONS

Allergic sensitization has been reported following both oral and parenteral administration of folic acid. You may at 1-844-487-4883 or the FDA by calling 1-800-FDA-1088.

DOSAGE AND ADMINISTRATION

Usual adult dose is 1-2 softgels once daily with a meal, or as prescribed by a licensed medical practitioner. Patients should be advised to swallow Oveeza Softgels whole. Do not break open, crush, dissolve, or chew Oveeza Softgels. Do Not Exceed the Recommended Dosage.

HOW SUPPLIED

Oveeza Softgels are available as brown, oblong softgels imprinted with "404" and are available in 30-count bottles (73480-404-30*).

STORAGE

Store at 20°-25°C (68°-77°F); excursions permitted to 15°-30°C (59°-86°F) [See USP Controlled Room Temperature.] Protect from heat, light and moisture. Tamper Evident: Do not use if seal is broken or missing.

Oveeza Softgels - Dietary Supplement Dispensed by Prescription†

DOSAGE AND ADMINISTRATION

Supplement Facts
Serving Size: 2 Softgels | Servings per Bottle: 15
Amount Per Serving |  | %Daily Value
Folate (as folic acid) | 1,667 mcg DFE (1 mg Folic Acid) | 417%
Vitamin B12 (as methylcobalamin) | 500 mcg | 20,834%
Alpha Lipoic Acid (ALA) | 100 mg | [Daily Values (DV) not established.]
CoEnzyme Q-10 (ubiquinone) | 100 mg
Total Omega-3 Fatty Acids | 1125 mg
Eicosapentaenoic Acid (EPA) | 600 mg
Docosahexaenoic Acid (DHA) | 450 mg

OTHER INGREDIENTS Lecithin, Beeswax, Gelatin (Bovine), Glycerin, Annatto Ext, Titanium Dioxide, Puriﬁed water. CONTAINS: Fish and Soy.

PRINCIPAL DISPLAY PANEL - 30 Softgel Bottle Label

73480-404-30

OVEEZA
Softgels

Dietary Supplement

Dispensed by Prescription

30 Softgels

TRIVUE
PHARMACEUTICALS, INC.